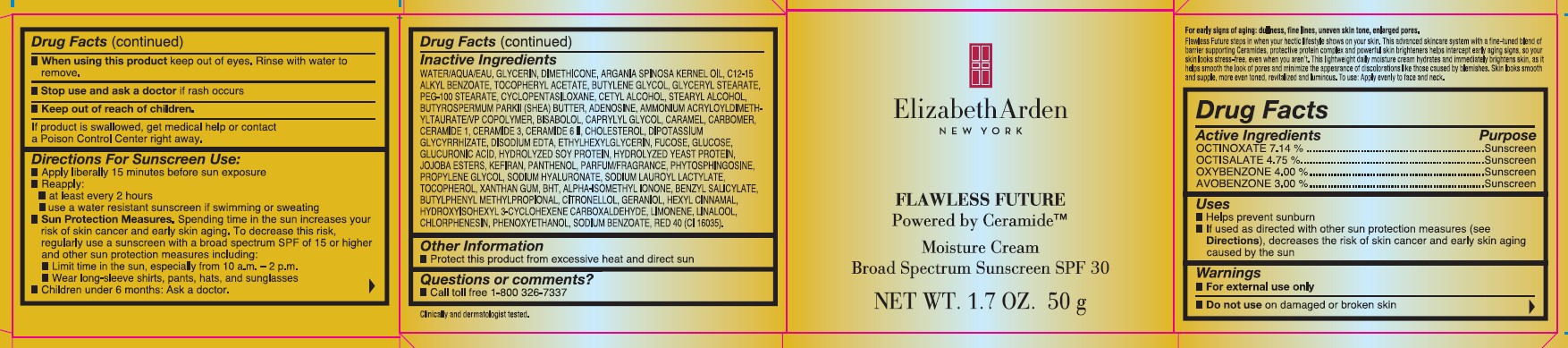 DRUG LABEL: FLAWLESS FUTURE SPF 30
NDC: 10967-683 | Form: EMULSION
Manufacturer: REVLON
Category: otc | Type: HUMAN OTC DRUG LABEL
Date: 20251229

ACTIVE INGREDIENTS: OCTINOXATE 7.14 mg/1 g; OXYBENZONE 4 mg/1 g; OCTISALATE 4.75 mg/1 g; AVOBENZONE 3 mg/1 g
INACTIVE INGREDIENTS: JOJOBA OIL, RANDOMIZED; KEFIRAN; CAPRYLYL GLYCOL; CARAMEL; CHOLESTEROL; GLYCYRRHIZINATE DIPOTASSIUM; ISOMETHYL-.ALPHA.-IONONE; STEARYL ALCOHOL; WATER; GLYCERIN; ARGAN OIL; PEG-100 STEARATE; ANHYDROUS DEXTROSE; HYDROLYZED SOY PROTEIN (ENZYMATIC; 2000 MW); SHEA BUTTER; CYCLOMETHICONE 5; CETYL ALCOHOL; CERAMIDE 1; CERAMIDE 6 II; EDETATE DISODIUM ANHYDROUS; ETHYLHEXYLGLYCERIN; BENZYL SALICYLATE; BUTYLENE GLYCOL; DIMETHICONE; ALKYL (C12-15) BENZOATE; ALPHA-TOCOPHEROL ACETATE; GLYCERYL MONOSTEARATE; PHYTOSPHINGOSINE; PROPYLENE GLYCOL; HYALURONATE SODIUM; TOCOPHEROL; .BETA.-CITRONELLOL, (R)-; SODIUM LAUROYL LACTYLATE; XANTHAN GUM; BUTYLATED HYDROXYTOLUENE; BUTYLPHENYL METHYLPROPIONAL; CHLORPHENESIN; HYDROXYISOHEXYL 3-CYCLOHEXENE CARBOXALDEHYDE; LIMONENE, (+)-; PHENOXYETHANOL; HYDROLYZED WHEAT PROTEIN (ENZYMATIC, 3000 MW); FUCOSE; LINALOOL, (+/-)-; SODIUM BENZOATE; ADENOSINE; AMMONIUM ACRYLOYLDIMETHYLTAURATE/VP COPOLYMER; LEVOMENOL; CARBOMER HOMOPOLYMER, UNSPECIFIED TYPE; CERAMIDE 3; GERANIOL

FLAWLESS FUTURE MOISTURE CREAM BROAD SPECTRUM SUNSCREEN SPF 30

ACTIVE INGREDIENTS

OCTINOXATE 7.14%

OCTISALATE 4.75%

OXYBENZONE 4.00%

AVOBENZONE 3.00%

OTHER INGREDIENTS

WATER/AQUA/EAU, GLYCERIN, DIMETHICONE, ARGANIA SPINOSA KERNEL OIL, C12-15 ALKYL BENZOATE, TOCOPHERYL ACETATE, BUTYLENE GLYCOL, GLYCERYL STEARATE, PEG-100 STEARATE, CYCLOPENTASILOXANE, CETYL ALCOHOL, STEARYL ALCOHOL, BUTYROSPERMUM PARKII (SHEA) BUTTER, ADENOSINE, AMMONIUM ACRYLOYLDIMETHYLTAURATE/VP COPOLYMER, BISABOLOL, CAPRYLYL GLYCOL, CARAMEL, CARBOMER, CERAMIDE 1, CERAMIDE 3, CERAMIDE 6 II, CHOLESTEROL, DIPOTASSIUM GLYCYRRHIZATE, DISODIUM EDTA, ETHYLHEXYLGLYCERIN, FUCOSE, GLUCOSE, GLUCURONIC ACID, HYDROLYZED SOY PROTEIN, HYDROLYZED YEAST PROTEIN, JOJOBA ESTERS, KEFIRAN, PANTHENOL, PARFUM/FRAGRANCE, PHYTOSPHINGOSINE, PROPYLENE GLYCOL, SODIUM HYALURONATE, SODIUM LAUROYL LACTYLATE, TOCOPHEROL, XANTHAN GUM, BHT, ALPHA-ISOMETHYL IONONE, BENZYL SALICYLATE, BUTYLPHENYL METHYLPROPIONAL, CITRONELLOL, GERANIOL, HEXYL CINNAMAL, HYDROXYISOHEXYL 3-CYCLOHEXENE CARBOXALDEHYDE, LIMONENE, LINALOOL, CHLORPHENESIN, PHENOXYETHANOL, SODIUM BENZOATE, RED 40 (CI 16035)

USES

- Helps prevent sunburn
- if used as directed with other sun protection measures (see Directions), decreases the risk of skin cancer and early skin aging caused by the sun.

WARNINGS

- For external use only
- Do not use on damaged or broken skin
- When using this product keep out of eyes. Rinse with water to remove.
- Stop use and ask a doctor if rash occurs
- keep out of reach of children.

If product is swallowed, get medical help or contact a Poison Control Center right away.

DIRECTIONS FOR SUNSCREEN USE

- Apply liberally 15 minutes before sun exposure
- Reapply:

- at least every 2 hours

- use a water resistant sunscreen if swimming or sweating

- Sun Protection Measures. Spending time in the sun increases your risk of skin cancer and early skin aging. To decrease this risk, regularly use a sunscreen with a broad spectrum SPF of 15 or higher and other sun protection measures including:

- Limit time in the sun, especially from 10 a.m. - 2 p.m.

- Wear long-sleeve shirts, pants, hats, and sunglasses

- Children under 6 months: Ask a doctor.

DOSAGE AND ADMINISTRATION

- Apply liberally 15 minutes before sun exposure
- Reapply at least every 2 hours

INDICATIONS AND USAGE

- Helps prevent sunburn
- If used as directed with other sun protection measures (see Directions), decreases the risk of skin cancer and early skin againg caused by the sun

Keep Out of Reach of Children. If product is swallowed, get medical help or contact a poison control center right away.

PURPOSE

Sunscreen

WARNINGS

- For external use only.
- Do not use on damaged or broken skin.
- When using this product keep out of eyes. Rinse with water to remove.
- Stop using and ask a doctor if rash occurs.